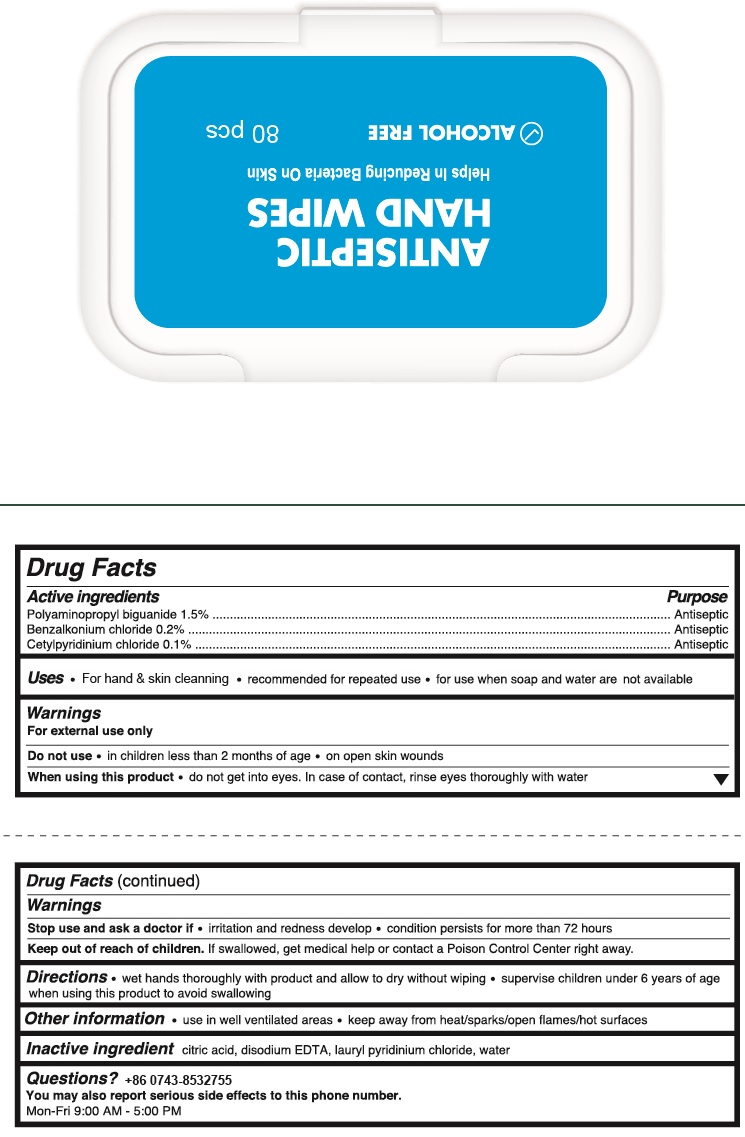 DRUG LABEL: antiseptic hand wipes
NDC: 78724-008 | Form: SWAB
Manufacturer: Jiebao Daily Chemical (Xiangxi)Co.,Ltd
Category: otc | Type: HUMAN OTC DRUG LABEL
Date: 20200731

ACTIVE INGREDIENTS: POLYAMINOPROPYL BIGUANIDE 15 mg/1 g; BENZALKONIUM CHLORIDE 2 mg/1 g; CETYLPYRIDINIUM CHLORIDE 1 mg/1 g
INACTIVE INGREDIENTS: water; EDETATE DISODIUM; LAURYLPYRIDINIUM CHLORIDE

Wipes

Active Ingredient

POLYAMINOPROPYL BIGUANIDE 1.5%

BENZALKONIUM CHLORIDE 0.2%

CETYLPYRIDINIUM CHLORIDE 0.1%

Purpose

Antiseptic

USE

- For hand and skin cleaning
- Recommended for repeated use
- For use when soap and water are not available

Warning

- For external use only.
- When using this product, Do not use into eyes. In case of contact, rinse eyes thoroughly with water.

- Stop use and ask a doctor, if irritation and redness develops; Condition persists for more than 72 hours
- Do not use In children less than 2 months of age; On open skin wounds.

Other Information：

use in well ventilated areas; keep away from heat/sparks//open flames/hot surfaces

KEEP OUT OF REACH OF CHILDREN

If swallowed, get medical help or contact a Poison Contrl Center right away.

Directions

- wet hands thoroughly with product and allow to dry without wiping
- supervise children under 6 years of age when using this product to avoid swallowing.

Inactive ingredients

citric acid, disodium EDTA, Lauryl Pyridinium chloride, water